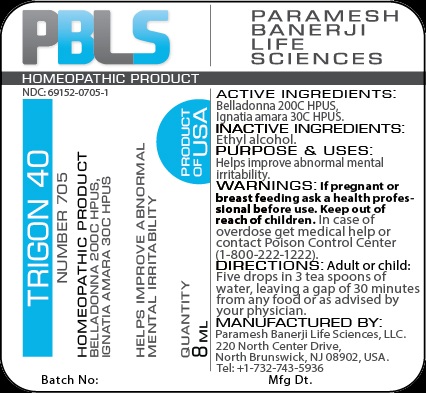 DRUG LABEL: Trigon 40 Number 705
NDC: 69152-0705 | Form: LIQUID
Manufacturer: Paramesh Banerji Life Sciences LLC
Category: homeopathic | Type: HUMAN OTC DRUG LABEL
Date: 20151016

ACTIVE INGREDIENTS: ATROPA BELLADONNA 200 [hp_C]/1 mL; STRYCHNOS IGNATII SEED 30 [hp_C]/1 mL
INACTIVE INGREDIENTS: ALCOHOL

Active Ingredients

Belladonna 200C HPUS, Ignatia amara 30C HPUS

Inactive Ingredient

Ethyl alcohol

Purpose

Helps improve abnormal mental irritability

Uses

Helps improve abnormal mental irritability

Warnings

If pregnant or breast feeding ask a health professional before use.

Keep out of reach of children. In case of overdose, get medical help or contact a Poison Control Center (1-800-222-1222) right away.

Direction

Adult or child: Five drops in 3 tea spoons of water, leaving a gap of 30 minutes from any food or as advised by your physician.

Manufactured by

Paramesh Banerji Life Sciences, LLC

220 North Center Drive

North Brunswick, NJ 08902, USA

Tel: +1-732-743-5936

Principal Display Panel

Homeopathic Product

NDC: 69152-0705-1

Trigon 40

Homeopathic Product

Belladonna 200C HPUS, Ignatia amara 30C HPUS

Helps improve abnormal mental irritability

Quantity

8mL

Product of USA